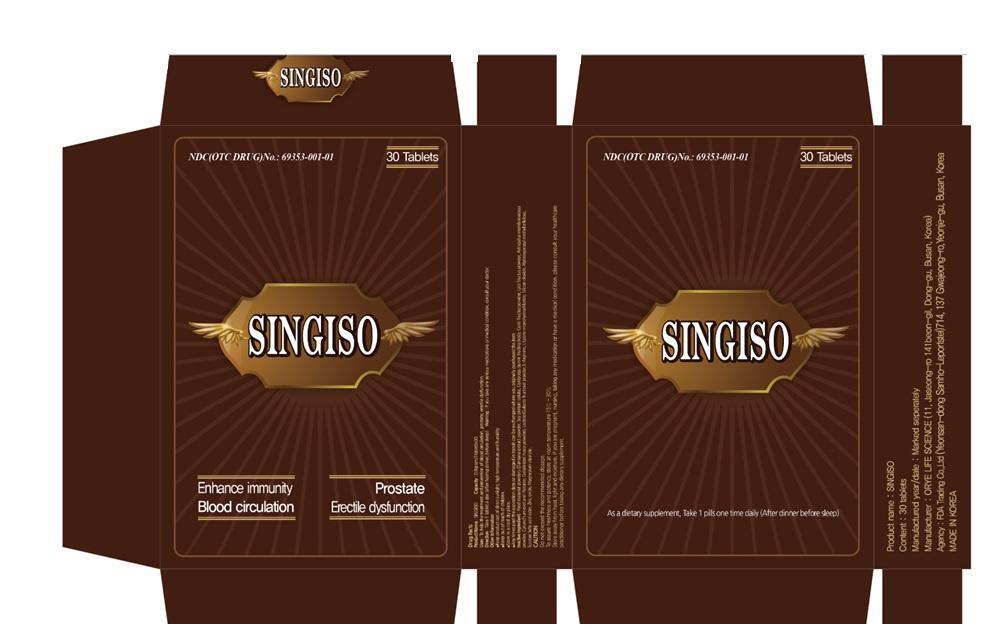 DRUG LABEL: Singiso
NDC: 69353-001 | Form: TABLET
Manufacturer: FDA TRADING CO.,LTD.
Category: otc | Type: HUMAN OTC DRUG LABEL
Date: 20141112

ACTIVE INGREDIENTS: ASIAN GINSENG 0.125 g/1 1
INACTIVE INGREDIENTS: TURNERA DIFFUSA LEAF; SOY PROTEIN; CORDYCEPS GUNNII FRUITING BODY; CORNUS OFFICINALIS FRUIT; LYCIUM BARBARUM FRUIT; ASTRAGALUS PROPINQUUS ROOT; CYNANCHUM STAUNTONII ROOT; LEPIDIUM MEYENII WHOLE; LACTOSE; ARGININE; LYSINE HYDROCHLORIDE; SILICON DIOXIDE; HYPROMELLOSES; SUCROSE; ZINC OXIDE; MAGNESIUM STEARATE

Singiso

Active ingredients

Red ginseng 15.63%

PURPOSE

Stimulant

Keep out of reach of children

Uses

To help the treatment and prevention of blood circulation, prostate, erectile dysfunction.

Warning

if you take any serious medications or medical condition, consult your doctor

Direction

Take 1 tablet a day (after having dinner, before sleep)

Inactive Ingredient: Food material powders (Damiana extract powder, Soy protein isolate, Cordyceps gunnii fruiting body, Corni fructus powder, Lycii fructus powder, Astragalus membranaceus powder, Cynanchum root and rhizome, Gelatinized maca powder), Lactose (Galacto fructose) powder, L‐Arginine, L‐Lysine monohydrochloride, Silicon dioxide, Hydroxypropyl methylcellulose, Sucrose fatty acid ester, Zinc oxide, Magnesium stearate.

Other Information

- Keep product out of direct sunlight, high temperature and humidity.
- Store in a cool dry place.
- Any times past the expiration date or damaged in transit can be exchanged where you originally purchased the item.

CAUTION:
Do not exceed the recommended dosage.
To assure freshness and potency, store at room temperature 15°C - 30°C
Store away from heat, light and moisture, if you are pregnant, nursing, taking any medication or have a medical condition, please consult your healthcare practitioner before taking any dietary supplement.